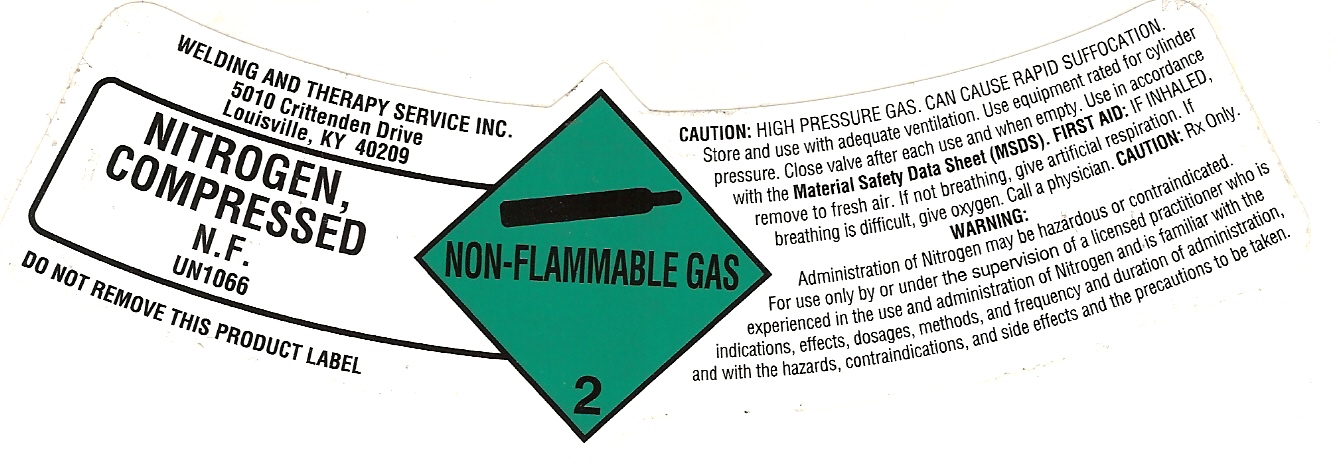 DRUG LABEL: Nitrogen
NDC: 33344-001 | Form: GAS
Manufacturer: Welding & Therapy Service Inc.
Category: prescription | Type: HUMAN PRESCRIPTION DRUG LABEL
Date: 20110722

ACTIVE INGREDIENTS: Nitrogen 99 L/100 L

NITROGEN COMPRESSED LABEL

PACKAGE LABEL

WELDING AND THERAPY SERVICE INC.
5010 CRITTENDEN DRIVE
LOUISVILLE, KY 40209
NITROGEN,
COMPRESSED
N.F.
UN1066
NON-FLAMMABLE GAS 2
DO NOT REMOVE THIS PRODUCT LABEL
CAUTION: HIGH PRESSURE GAS. CAN CAUSE RAPID SUFFOCATION.
Store and use with adequate ventilation. Use equipment rated for cylinder
pressure. Close valve after each use and when empty. Use in accordance
with the Material Safety Data Sheet (MSDS). FIRST AID: IF INHALED,
remove to fresh air. if not breathing, give artificial respiration. If
breathing is difficult, give oxygen. Call a physician. CAUTION: Rx Only.
WARNING:
Administration of Nitrogen may be hazardous or contraindicated.
For use only by or under the supervision of a licensed practitioner who is
experienced in the use and administration of Nitrogen and is familiar with the
indications, effects, dosages, methods, and frequency and duration of administration,
and with the hazards, contraindications, and side effects and the precautions to be taken.